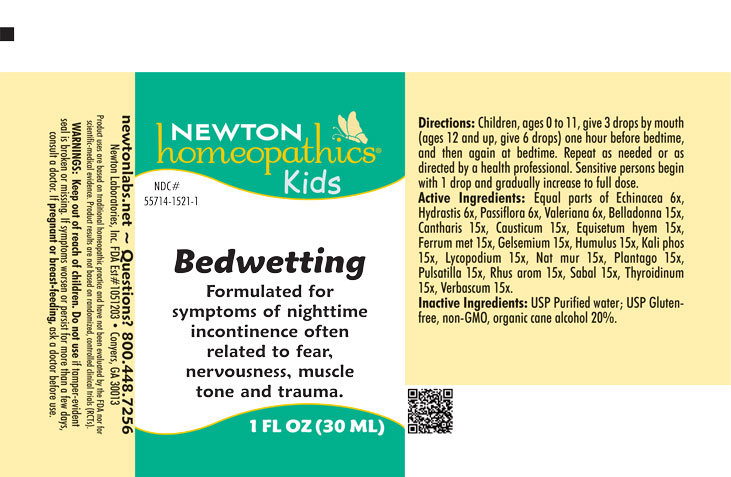 DRUG LABEL: Bedwetting
NDC: 55714-1521 | Form: LIQUID
Manufacturer: Newton Laboratories, Inc.
Category: homeopathic | Type: HUMAN OTC DRUG LABEL
Date: 20250724

ACTIVE INGREDIENTS: ECHINACEA, UNSPECIFIED 6 [hp_X]/1 mL; VALERIAN 6 [hp_X]/1 mL; ATROPA BELLADONNA 15 [hp_X]/1 mL; LYTTA VESICATORIA 15 [hp_X]/1 mL; CAUSTICUM 15 [hp_X]/1 mL; EQUISETUM HYEMALE 15 [hp_X]/1 mL; IRON 15 [hp_X]/1 mL; GELSEMIUM SEMPERVIRENS ROOT 15 [hp_X]/1 mL; HOPS 15 [hp_X]/1 mL; DIBASIC POTASSIUM PHOSPHATE 15 [hp_X]/1 mL; GOLDENSEAL 6 [hp_X]/1 mL; SODIUM CHLORIDE 15 [hp_X]/1 mL; PLANTAGO MAJOR 15 [hp_X]/1 mL; ANEMONE PULSATILLA 15 [hp_X]/1 mL; TOXICODENDRON PUBESCENS LEAF 15 [hp_X]/1 mL; SAW PALMETTO 15 [hp_X]/1 mL; THYROID, UNSPECIFIED 15 [hp_X]/1 mL; VERBASCUM THAPSUS 15 [hp_X]/1 mL; PASSIFLORA INCARNATA FLOWERING TOP 6 [hp_X]/1 mL; LYCOPODIUM CLAVATUM SPORE 15 [hp_X]/1 mL
INACTIVE INGREDIENTS: ALCOHOL; WATER

Bedwetting 1521L

INDICATIONS & USAGE SECTION

Formulated for symptoms of nighttime incontinence often related to fear, nervousness, muscle tone and trauma.

OTC - ACTIVE INGREDIENT SECTION

Equal parts of Echinacea 6x, Hydrastis canadensis 6x, Passiflora incarnata 6x, Valeriana officinalis 6x, Belladonna 15x, Cantharis 15x, Causticum 15x, Equisetum hyemale 15x, Ferrum metallicum 15x, Gelsemium sempervirens 15x, Humulus lupulus 15x, Kali phosphoricum 15x, Lycopodium clavatum 15x, Natrum muriaticum 15x, Plantago major 15x, Pulsatilla 15x, Rhus aromatica 15x, Sabal serrulata 15x, Thyroidinum 15x, Verbascum thapsus 15x.

OTC - PURPOSE SECTION

Formulated for associated symptoms often related to fear, nervousness, muscle tone and trauma.

INACTIVE INGREDIENT SECTION

USP Purified Water; USP Gluten-free, non-GMO, organic cane alcohol 20%.

QUESTIONS SECTION

newtonlabs.net – Questions? 800.448.7256

Newton Laboratories, Inc. FDA Est # 1051203 - Conyers, GA 30013

WARNINGS SECTION

WARNINGS: Keep out of reach of children. Do not use if tamper-evident seal is broken or missing. If symptoms worsen or persist for more than a few days, consult a doctor. If pregnant or breast-feeding, ask a doctor before use.

OTC - PREGNANCY OR BREAST FEEDING SECTION

If pregnant or breast-feeding, ask a doctor before use.

OTC - KEEP OUT OF REACH OF CHILDREN SECTION

Keep out of reach of children.

DOSAGE & ADMINISTRATION SECTION

Directions: Children, ages 0 to 11, give 3 drops by mouth (ages 12 and up, give 6 drops) one hour before bedtime, and then again at bedtime. Repeat as needed or as directed by a health professioal. Sensitive person begin with 1 drop and gradually increase to full dose.